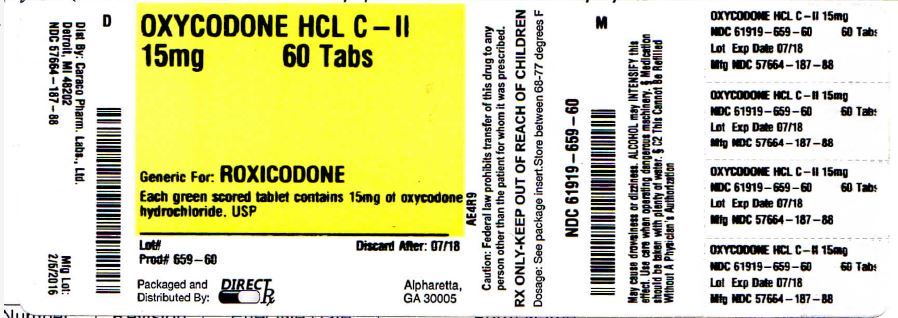 DRUG LABEL: Oxycodone HCL
NDC: 61919-659 | Form: TABLET
Manufacturer: Direct RX
Category: prescription | Type: HUMAN PRESCRIPTION DRUG LABEL
Date: 20160208
DEA Schedule: CII

ACTIVE INGREDIENTS: OXYCODONE HYDROCHLORIDE 15 mg/1 1
INACTIVE INGREDIENTS: ANHYDROUS LACTOSE; CELLULOSE, MICROCRYSTALLINE; STARCH, CORN; SODIUM STARCH GLYCOLATE TYPE A POTATO; FD&C BLUE NO. 2; SILICON DIOXIDE; MAGNESIUM STEARATE; D&C YELLOW NO. 10

OXYCODONE HCL